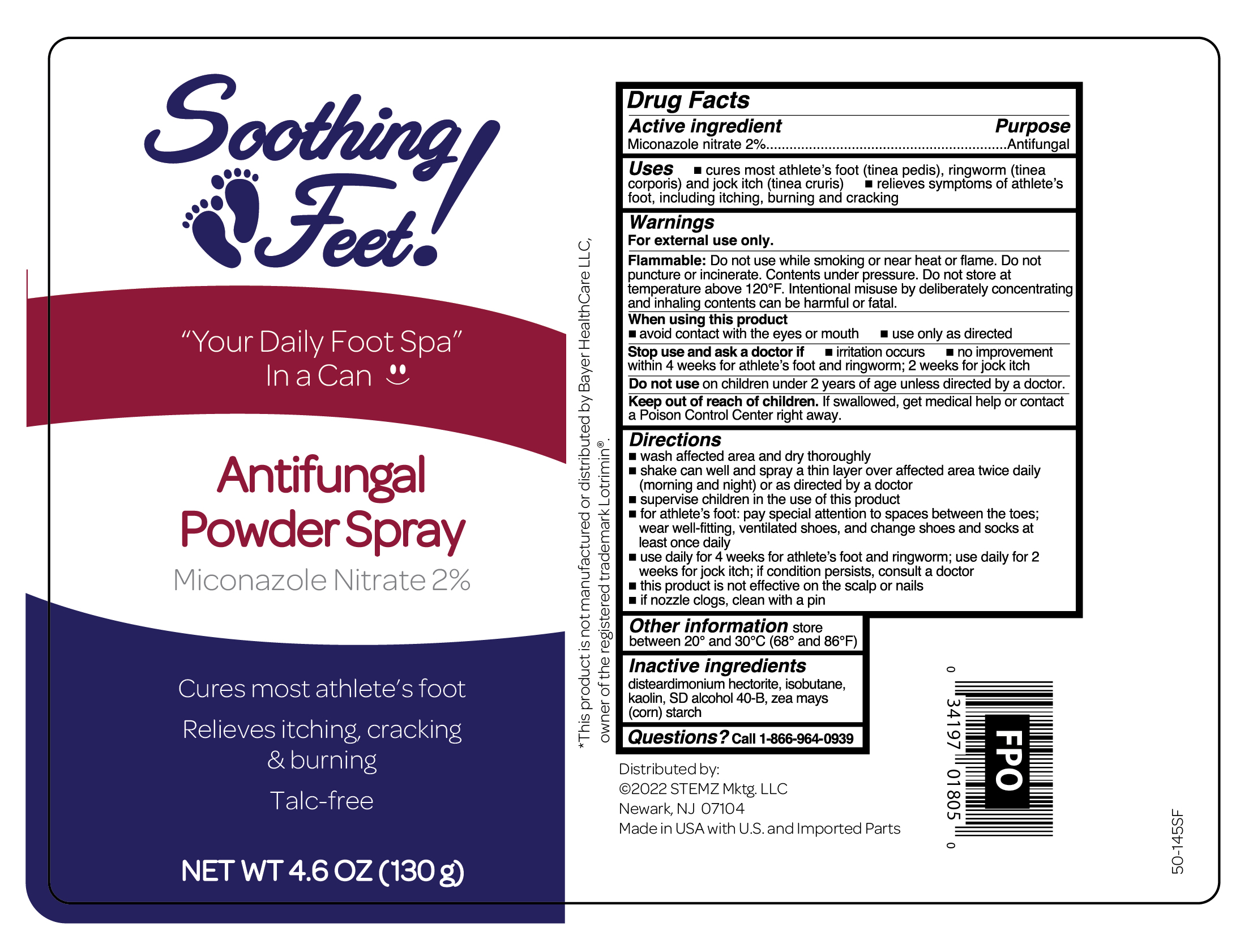 DRUG LABEL: Miconazole Nitrate
NDC: 56104-907 | Form: AEROSOL, POWDER
Manufacturer: Premier Brands of America Inc.
Category: otc | Type: HUMAN OTC DRUG LABEL
Date: 20251106

ACTIVE INGREDIENTS: MICONAZOLE NITRATE 20 mg/1 g
INACTIVE INGREDIENTS: ALCOHOL; ZEA MAYS (CORN) STARCH; ISOBUTANE; KAOLIN; DISTEARDIMONIUM HECTORITE

Soothing Feet Antifungal Miconazole Antifungal Powder Spray Talc-Free

Active ingredient

Miconazole nitrate 2%

Purpose

Antifungal

Uses

- cures most athlete's foot (tinea pedis), ringworm (tinea corporis) and jock itch (tinea cruris)
- relieves symptoms of athlete's foot, including itching, burning and cracking

Warnings

For external use only.

Flammable:

Do not use while smoking or near heat or flame. Do not puncture or incinerate. Contents under pressure. Do not store at temperature above 120ºF. Intentional misuse by deliberately concentrating and inhaling contents can be harmful or fatal.

When using this product

- avoid contact with the eyes or mouth
- use only as directed

Stop use and ask a doctor if

- irritation occurs
- no improvement within 4 weeks for athlete's foot and ringworm; 2 weeks for jock itch

Do not use

on children under 2 years of age unless directed by a doctor.

Keep out of reach of children.

If swallowed, get medical help or contact a Poison Control Central right away.

Directions

- wash the affected area and dry thoroughly
- shake can well and spray a thin layer of the product over affected area twice daily (morning and night) or as directed by a doctor
- supervise children in the use of this product
- for athlete's foot: pay special attention to spaces between the toes; wear well-fitting, ventilated shoes, and change shoes and socks at least once daily
- use daily for 4 weeks for athlete's foot and ringworm; use daily for 2 weeks for jock itch; if conditions persist, consult a doctor
- this product is not effective on the scalp or nails
- if nozzle clogs, clean with a pin

Other information

- store between 20º and 30ºC (68º and 86ºF)

Inactive ingredients

DISTEARDIMONIUM HECTORITE, ISOBUTANE, KAOLIN, SD ALCOHOL 40-B, ZEA MAYS (CORN) STARCH,

Questions?

Call 1-866-964-0939

RECENT MAJOR CHANGES

..

Principal Display Panel

Soothing

Feet!

"Your Daily Foot Spa"

In a Can

Antifungal

Powder Spray

Miconazole Nitrate 2%

Cures most athlete's foot

Relieves itching,cracking

& burning

Talc- free

NET WT 4.6 OZ. (130 g)